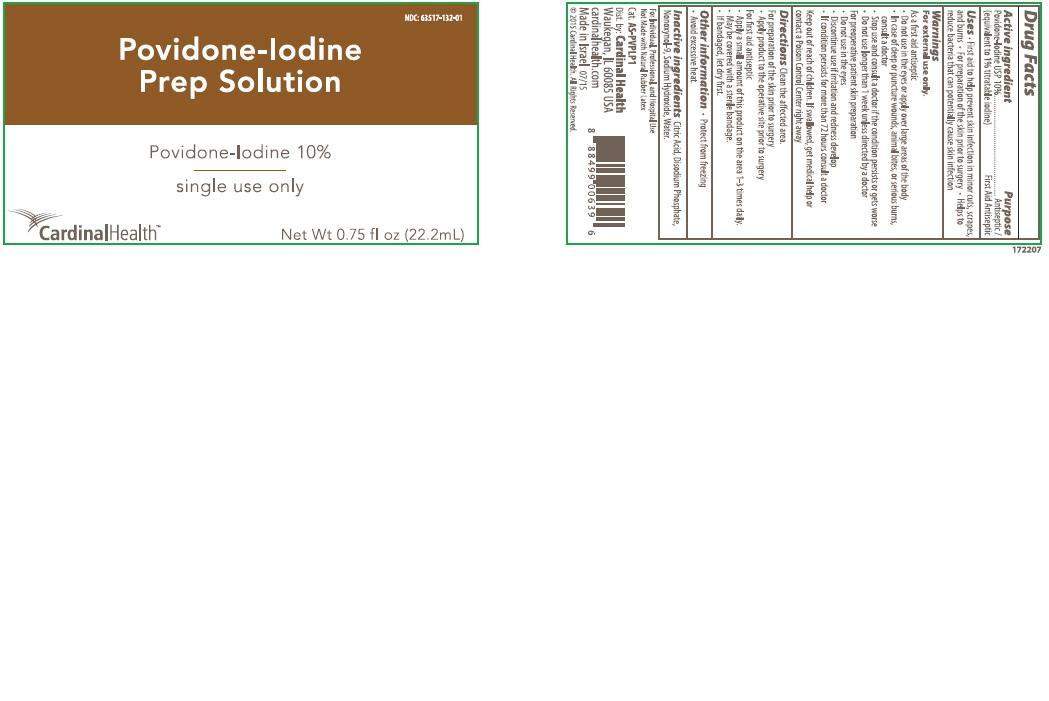 DRUG LABEL: Povidone Iodine Prep
NDC: 63517-132 | Form: SOLUTION
Manufacturer: Cardinal Health
Category: otc | Type: HUMAN OTC DRUG LABEL
Date: 20221212

ACTIVE INGREDIENTS: POVIDONE-IODINE 1 g/100 mL
INACTIVE INGREDIENTS: NONOXYNOL-9; WATER; SODIUM PHOSPHATE, DIBASIC, ANHYDROUS; CITRIC ACID MONOHYDRATE; SODIUM HYDROXIDE

Drug Facts

Active ingredient

Povidone Iodine 10%

(equivalent to 1% titratable iodine)

Purpose

Antiseptic/First Aid Antispetic

Uses

- First aid to help prevent skin infection in minor cuts,scrapes, and burns
- For preparation of the skin prior to skin surgery
- Helps to reduce bacteria that can potentially cause skin infection

Warnings

For External Use Only.

Do not use

As a first aid antiseptic

- Do not use in the eyes or apply over large areas of the body
- In case of deep or puncture wounds, animal bites, or serious burns, consult a doctor
- Stop use and consult a doctor if the condition persists or gets worse
- Do not use longer than 1 week unless directed by a doctor

For preoperative patient skin preparation

- Do not use in the eyes
- Discontinue use if irritation and redness develop
- If condition persists for more than 72 hours, consult a doctor

Keep out of reach of children.

- If swallowed, get medical help or contact a Poison Control Center right away.

Directions:

Clean the affected area.

For preparation of skin prior to surgery

- Apply product to the operative site prior to surgery

For first aid antiseptic

- Apply a small amount of this product on the area 1-3 times daily.
- May be covered with a sterile bandage.
- If bandaged, let dry first.

Other information

- Protect from freezing
- Avoid excessive heat

Inactive Ingredients:

Citric Acid, Disodium Phosphate, Nonoxynol-9, Sodium Hydroxide, Water

Principal Display Panel

Povidone-Iodine Prep Solution

Povidone-Iodine 10%

single use only

Cardinal Health

Net Wt. 0.75 fl oz (22.2 mL)

NDC 63517-132-01